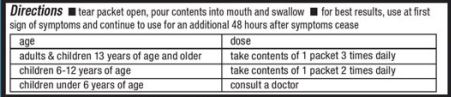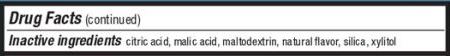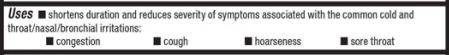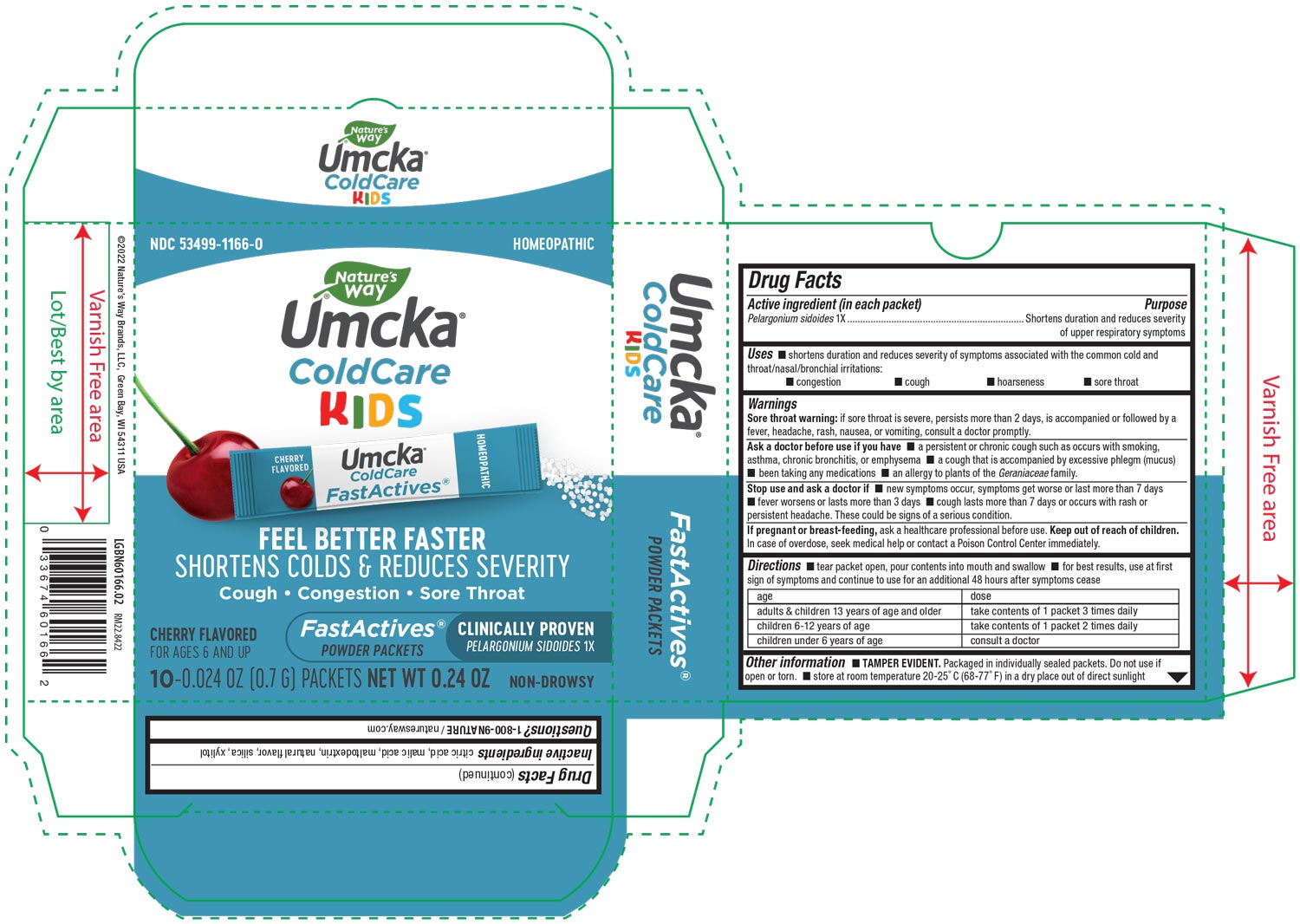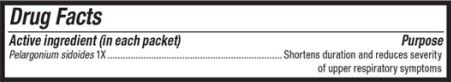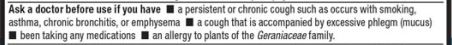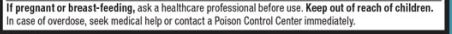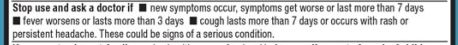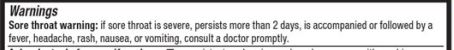 DRUG LABEL: Umcka FastActives Cherry
NDC: 83102-1166 | Form: POWDER
Manufacturer: ProSolutions Inc.
Category: homeopathic | Type: HUMAN OTC DRUG LABEL
Date: 20250410

ACTIVE INGREDIENTS: PELARGONIUM SIDOIDES ROOT 1 [hp_X]/700 mg
INACTIVE INGREDIENTS: SILICON DIOXIDE; XYLITOL; MALIC ACID; MALTODEXTRIN; CITRIC ACID MONOHYDRATE

Umcka FastActives Cherry